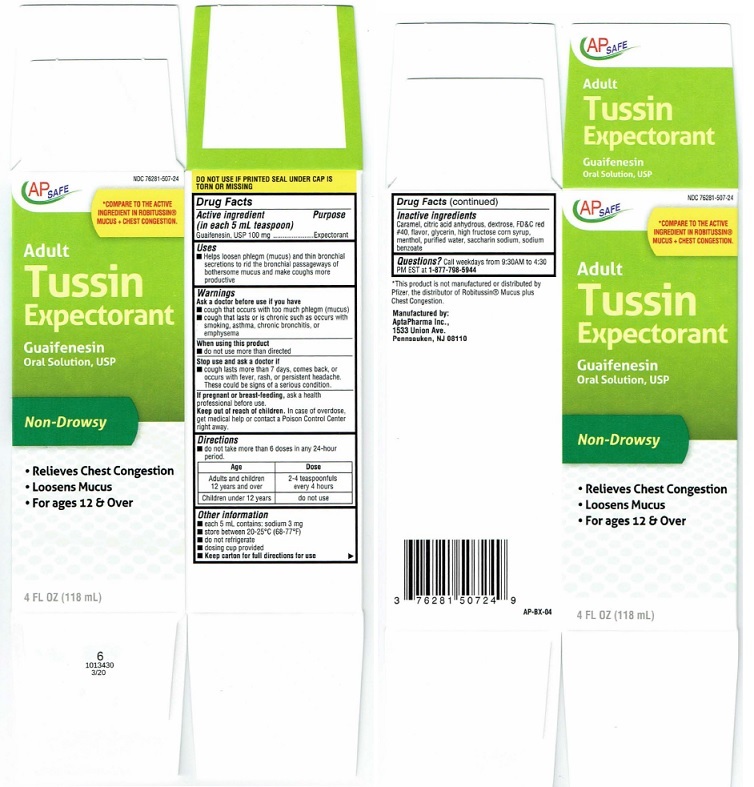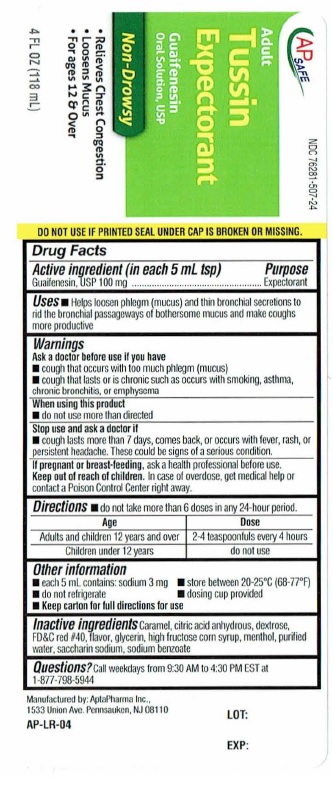 DRUG LABEL: Tussin Expectorant
NDC: 76281-507 | Form: LIQUID
Manufacturer: AptaPharma, Inc.
Category: otc | Type: HUMAN OTC DRUG LABEL
Date: 20251226

ACTIVE INGREDIENTS: GUAIFENESIN 100 mg/5 mL
INACTIVE INGREDIENTS: CARAMEL; ANHYDROUS CITRIC ACID; DEXTROSE; FD&C RED NO. 40; GLYCERIN; HIGH FRUCTOSE CORN SYRUP; MENTHOL; WATER; SACCHARIN SODIUM; SODIUM BENZOATE

Drug Facts

Active ingredient (in each 5 mL teaspoon)
Guaifenesin, USP ........ 100 mg

Purpose
Expectorant

Uses
■ Helps loosen phlegm (mucus) and thin bronchial
secretions to rid the bronchial passageways of
bothersome mucus and make coughs more
productive

Warnings

Ask a doctor before use if you have
■ cough that occurs with too much phlegm (mucus)
■ cough that lasts or is chronic such as occurs with
smoking, asthma, chronic bronchitis, or
emphysema

When using this product
■ do not use more than directed

Stop use and ask a doctor if
■ cough lasts more than 7 days, comes back, or
occurs with fever, rash, or persistent headache.
These could be signs of a serious condition.

If pregnant or breast·feeding, ask ahealth
professional before use.

Keep out of reach of children.In case of overdose,
get medicai help or contact a Poison Control Center
right away.

Directions
■ do not take more than 6 doses in any 24-hour
period.

Age | Dose
Adults and children; 12 years and over | 2-4 teaspoonfuls; every 4 hours
Children under 12 years | do not use

Other information
■ each 5 mL contains: sodium 3 mg
■ store between 20-2SoC (68-77°F)
■ do not refrigerate
■ dosing cup provided
■ Keep carton for full directions for use

Inactive ingredients

Caramel, citric acid anhydrous, dextrose, FD&C red
#40, flavor, glycerin, high fructose corn syrup,
menthol, purified water, saccharin sodium, sodium
benzoate

QUESTIONS

Questions? Call weekdays from 9:30AM to 4:30
PM EST at 1-877-798-5944

Package Label

AP SAFE NDC 76281-507-24

*COMPARE TO THE ACTIVE
INGREDIENT IN ROBITUSSIN®
MUCUS+CHEST CONGESTION.

Adult
Tussin
Expectorant

Guaifenesin
Oral Solution, USP
Non-Drowsy

• Relieves Chest Congestion
• Loosens Mucus
• For ages 12 & Over

4 FL OZ (118 mL)

DO NOT USE IF PRINTED SEAL UNDER CAP IS
TORN OR MISSING

AP-BX-04

*This product is not manutactured or distributed by
Pfizer, the distributor of Robitussin®Mucus plus
Chest Congestion.

Manufactured by:
AplaPharma Inc.,
1533 Union Ave.
Pennsauken, NJ 08110

Carton

Bottle

res